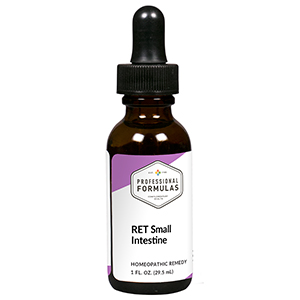 DRUG LABEL: RET Small Intestine
NDC: 63083-7010 | Form: LIQUID
Manufacturer: Professional Complementary Health Formulas
Category: homeopathic | Type: HUMAN OTC DRUG LABEL
Date: 20190815

ACTIVE INGREDIENTS: CICHORIUM INTYBUS FLOWER 3 [hp_X]/29.5 mL; CLEMATIS VITALBA FLOWER 3 [hp_X]/29.5 mL; ORNITHOGALUM UMBELLATUM FLOWERING TOP 3 [hp_X]/29.5 mL; SODIUM PHOSPHATE, DIBASIC, HEPTAHYDRATE 3 [hp_X]/29.5 mL; GOLD 30 [hp_X]/29.5 mL; POTASSIUM DICHROMATE 30 [hp_X]/29.5 mL; LIQUID PETROLEUM 30 [hp_X]/29.5 mL; PHOSPHORUS 30 [hp_X]/29.5 mL; SCABIES LESION LYSATE (HUMAN) 30 [hp_X]/29.5 mL; PULSATILLA MONTANA WHOLE 30 [hp_X]/29.5 mL; DATURA STRAMONIUM 30 [hp_X]/29.5 mL
INACTIVE INGREDIENTS: ALCOHOL; WATER

RET10

ACTIVE INGREDIENTS

Chicory flower essence 3X
Clematis flower essence 3X
Star of Bethlehem flower essence 3X
Natrum phosphoricum 3X, 6X, 30X
and all the following at 30X, 100X, 200X:
Aurum metallicum
Kali bichromicum
Petroleum
Phosphorus
Psorinum
Pulsatilla
Stramonium

QUESTIONS

Professional Formulas

PO Box 2034 Lake Oswego, OR 97035

INDICATIONS

Temporarily relieves being withdrawn or living in ones own world, stress following trauma, fear, being self-centered, being easily offended, or self-pity.*

PURPOSE

*Claims based on traditional homeopathic practice, not accepted medical evidence. Not FDA evaluated.

WARNINGS

In case of overdose, get medical help or contact a poison control center right away.

Keep out of the reach of children.

PREGNANCY OR BREAST FEEDING

If pregnant or breastfeeding, ask a healthcare professional before use.

DIRECTIONS

Place drops under tongue 30 minutes before/after meals. Adults and children 12 years and over: Take 5 drops up to 4 times per day for up to one month. Consult a physician for use in children under 12 years of age.

OTHER INFORMATION

Tamper resistant. If seal is broken, do not use. After opening, close container tightly and store at room temperature away from heat.

INACTIVE INGREDIENTS

20% ethanol, purified water.

LABEL

Est 1985

Professional Formulas

Complementary Health

RET Small Intestine

Homeopathic Remedy

1 FL. OZ. (29.5 mL)